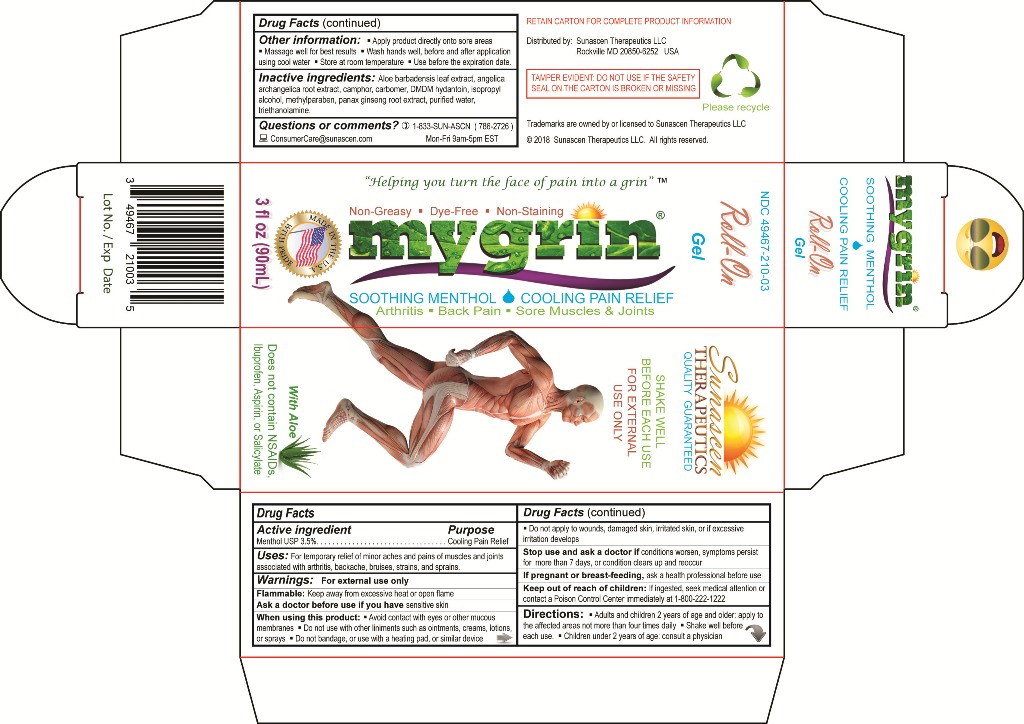 DRUG LABEL: MYGRIN Roll-On
NDC: 49467-210 | Form: GEL
Manufacturer: Sunascen Therapeutics LLC
Category: otc | Type: HUMAN OTC DRUG LABEL
Date: 20230131

ACTIVE INGREDIENTS: MENTHOL 35 mg/1 mL
INACTIVE INGREDIENTS: ANGELICA ARCHANGELICA ROOT; ALOE VERA LEAF; CAMPHOR (NATURAL); CARBOMER HOMOPOLYMER TYPE C; DMDM HYDANTOIN; ISOPROPYL ALCOHOL; METHYLPARABEN; ASIAN GINSENG; WATER; TROLAMINE

MYGRIN® Roll-On Gel (Menthol 3.5% USP)

ACTIVE INGREDIENTS

Menthol, USP 3.5%

PURPOSE

External Analgesic (Cooling Pain Relief)

INDICATIONS AND USAGE

For the temporary relief of minor aches and pains of muscles and joints associated with arthritis, backache, bruises, strains, and sprains.

WARNINGS

For external use only

Flammable

Keep away from excessive heat or open flame

When using this product,

- Avoid contact with eyes or other mucous membranes
- Do not use with other liniments such as ointments, creams, lotions, or sprays
- Do not apply to wounds, damaged skin, irritated skin, or if excessive irritation develops
- Do not bandage, or use with a heating pad, or similar device

Ask a doctor before use if you have,

- Sensitive skin

Stop use and ask a doctor if,

- Conditions worsens
- Symptoms persist for more than 7 days
- Condition clears up and reoccurs

If pregnant or breastfeeding,

ask a health professional before use.

Keep out of the reach of children

If ingested, seek medical attention or contact a Poison Control Center immediately at 1-800-222-1222.
Prompt medical attention is critical for adults as well as for children even if you do not notice any signs or symptoms.

DOSAGE AND ADMINISTRATION (Directions)

Adults and Children 2 years of age and older: Apply to the affected areas not more than four times daily.
Children under 2 years of age: Consult a Physician.
Shake well before each use.

KEEP OUT OF REACH OF CHILDREN

If ingested, seek medical help right away or contact a Poison Control Center immediately.
Call Poison Control at 1-800-222-1222.
Prompt medical attention is critical for adults as well as for children even if you do not notice any signs or symptoms.

OTHER INFORMATION

- Apply product directly onto sore areas
- Massage well for best results
- Wash hands well, before and after application using cool water
- Store at room temperature
- Use before the expiration date

INACTIVE INGREDIENTS

Aloe barbadensis leaf extract, angelica archangelica root extract, camphor, carbomer, DMDM hydantoin, isopropyl alcohol, methylparaben, panax ginseng root extract, purified water, triethanolamine.

QUESTIONS OR COMMENTS?

Sunascen Therapeutics LLC
Call us toll free at 1-833-SUNASCN (786-2726) Mon-Fri 9am-5pm EST.
Email us at ConsumerCare@Sunascen.com
More information is available on our website at www.sunascen.com

PRINCIPAL DISPLAY PANEL

Sunascen Therapeutics LLC

NDC 49467-210-03

MYGRIN® Roll-On Gel
SOOTHING MENTHOL - COOLING PAIN RELIEF
Arthritis, Back Pain, Sore Muscles & Joints
Non-Greasy, Dye-Free, and Non-Staining
With Aloe
3 fl oz (90mL)

SHAKE WELL BEFORE EACH USE
FOR EXTERNAL USE ONLY

Does not contain NSAIDs, Ibuprofen, Aspirin, or Salicylate

"Helping you turn the face of pain into a grin" ™

TAMPER EVIDENT: DO NOT USE IF THE SAFETY SEAL ON THE CARTON IS BROKEN OR MISSING

RETAIN CARTON FOR COMPLETE PRODUCT INFORMATION

Distributed by: Sunascen Therapeutics LLC, Rockville MD 20850-6252
© 2018 Sunascen Therapeutics LLC, All rights reserved.
Trademarks are owned by or licensed to Sunascen Therapeutics LLC

Sunascen Therapeutics LLC
Quality Guaranteed
Please Recycle